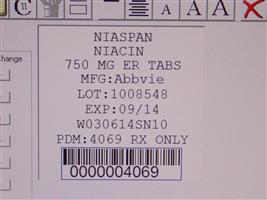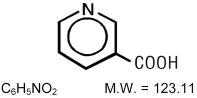 DRUG LABEL: Niaspan
NDC: 68151-4069 | Form: TABLET, FILM COATED, EXTENDED RELEASE
Manufacturer: Carilion Materials Management
Category: prescription | Type: HUMAN PRESCRIPTION DRUG LABEL
Date: 20130820

ACTIVE INGREDIENTS: NIACIN 750 mg/1 1
INACTIVE INGREDIENTS: TITANIUM DIOXIDE; FERRIC OXIDE RED; FD&C YELLOW NO. 6; FERRIC OXIDE YELLOW; HYPROMELLOSES; POLYETHYLENE GLYCOLS; POVIDONES; STEARIC ACID

HIGHLIGHTS OF PRESCRIBING INFORMATION

These highlights do not include all the information needed to use NIASPAN safely and effectively. See full prescribing information for NIASPAN. NIASPAN (niacin extended-release) tablet, film coated, extended release for oral use. Initial U.S. Approval: 1997®

RECENT MAJOR CHANGES

Indications and Usage: Limitations of Use (1) | 02/2013
Warnings and Precautions, Mortality and Coronary Heart Disease Morbidity (5.1) | 02/2013

1 INDICATIONS AND USAGE

NIASPAN contains extended-release niacin (nicotinic acid), and is indicated:

- To reduce elevated TC, LDL-C, Apo B and TG, and to increase HDL-C in patients with primary hyperlipidemia and mixed dyslipidemia. (1)
- In combination with simvastatin or lovastatin: to treat primary hyperlipidemia and mixed dyslipidemia when treatment with NIASPAN, simvastatin, or lovastatin monotherapy is considered inadequate. (1)
- To reduce the risk of recurrent nonfatal myocardial infarction in patients with a history of myocardial infarction and hyperlipidemia. (1)
- In combination with a bile acid binding resin:
  - Slows progression or promotes regression of atherosclerotic disease in patients with a history of coronary artery disease (CAD) and hyperlipidemia. (1)
  - As an adjunct to diet to reduce elevated TC and LDL-C in adult patients with primary hyperlipidemia. (1)
- To reduce TG in adult patients with severe hypertriglyceridemia. (1)

Limitations of use:

No incremental benefit of NIASPAN coadministered with simvastatin or lovastatin on cardiovascular morbidity and mortality over and above that demonstrated for niacin, simvastatin and lovastatin monotherapy, has been established.

NIASPAN, at doses of 1,500-2,000 mg/day, in combination with simvastatin, did not reduce the incidence of cardiovascular events more than simvastatin in a randomized controlled trial of patients with cardiovascular disease and mean baseline LDL-C levels of 74 mg per deciliter . (5.1)

2 DOSAGE AND ADMINISTRATION

- NIASPAN should be taken at bedtime with a low-fat snack. (2)
- Dose range: 500 mg to 2000 mg once daily. (2)
- Therapy with NIASPAN must be initiated at 500 mg at bedtime in order to reduce the incidence and severity of side effects which may occur during early therapy and should not be increased by more than 500 mg in any four week period. (2)
- Maintenance dose: 1000 to 2000 mg once daily. (2)
- Doses greater than 2000 mg daily are not recommended. (2)
- Concomitant therapy with lovastatin: Initial dose of lovastatin is 20 mg once a day; combination therapy with NIASPAN and lovastatin should not exceed doses of 2000 mg and 40 mg daily, respectively. (2)
- Concomitant therapy with simvastatin: Initial dose of simvastatin is 20 mg once a day; combination therapy with NIASPAN and simvastatin should not exceed doses of 2000 mg and 40 mg daily, respectively. (2)

3 DOSAGE FORMS AND STRENGTHS

Unscored film-coated tablets for oral administration: 500, 750 and 1000 mg niacin extended-release. (3)

4 CONTRAINDICATIONS

- Active liver disease, which may include unexplained persistent elevations in hepatic transaminase levels. , (45.3)
- Active peptic ulcer disease. (4)
- Arterial bleeding. (4)
- Known hypersensitivity to product components. , (46.1)

5 WARNINGS AND PRECAUTIONS

- Severe hepatic toxicity has occurred in patients substituting sustained-release niacin for immediate-release niacin at equivalent doses. (5.3)
- Myopathy has been reported in patients taking NIASPAN. The risk for myopathy and rhabdomyolysis are increased when lovastatin or simvastatin are coadministered with NIASPAN, particularly in elderly patients and patients with diabetes, renal failure, or uncontrolled hypothyroidism. (5.2)
- Liver enzyme abnormalities and monitoring: Persistent elevations in hepatic transaminase can occur. Monitor liver enzymes before and during treatment. (5.3)
- Use with caution in patients with unstable angina or in the acute phase of an MI. (5)
- NIASPAN can increase serum glucose levels. Glucose levels should be closely monitored in diabetic or potentially diabetic patients particularly during the first few months of use or dose adjustment. (5.4)

6 ADVERSE REACTIONS

Most common adverse reactions (incidence >5% and greater than placebo) are flushing, diarrhea, nausea, vomiting, increased cough, and pruritus. (6.1)

Flushing of the skin may be reduced in frequency or severity by pretreatment with aspirin (up to the recommended dose of 325 mg taken 30 minutes prior to NIASPAN dose). (2)

To report SUSPECTED ADVERSE REACTIONS, contact AbbVie Inc. at 1-800-633–9110 or FDA at 1-800-FDA-1088 or www.fda.gov/medwatch.

7 DRUG INTERACTIONS

- Statins: Caution should be used when prescribing niacin with statins as these agents can increase risk of myopathy/rhabdomyolysis. , (5.27.1)
- Bile Acid Sequestrants: Bile acid sequestrants have a high niacin-binding capacity and should be taken at least 4 - 6 hours before NIASPAN administration. (7.2)

8 USE IN SPECIFIC POPULATIONS

- Renal impairment: NIASPAN should be used with caution in patients with renal impairment. , (58.6)
- Hepatic impairment: NIASPAN is contraindicated in active liver disease or significant or unexplained hepatic dysfunction or unexplained elevations of serum transaminases. , , , (455.38.7)

FULL PRESCRIBING INFORMATION

1 INDICATIONS AND USAGE

Therapy with lipid-altering agents should be only one component of multiple risk factor intervention in individuals at significantly increased risk for atherosclerotic vascular disease due to hyperlipidemia. Niacin therapy is indicated as an adjunct to diet when the response to a diet restricted in saturated fat and cholesterol and other nonpharmacologic measures alone has been inadequate.

1. NIASPAN is indicated to reduce elevated TC, LDL-C, Apo B and TG levels, and to increase HDL-C in patients with primary hyperlipidemia and mixed dyslipidemia.
2. NIASPAN in combination with simvastatin or lovastatin is indicated for the treatment of primary hyperlipidemia and mixed dyslipidemia when treatment with NIASPAN, simvastatin, or lovastatin monotherapy is considered inadequate.
3. In patients with a history of myocardial infarction and hyperlipidemia, niacin is indicated to reduce the risk of recurrent nonfatal myocardial infarction.
4. In patients with a history of coronary artery disease (CAD) and hyperlipidemia, niacin, in combination with a bile acid binding resin, is indicated to slow progression or promote regression of atherosclerotic disease.
5. NIASPAN in combination with a bile acid binding resin is indicated to reduce elevated TC and LDL-C levels in adult patients with primary hyperlipidemia.
6. Niacin is also indicated as adjunctive therapy for treatment of adult patients with severe hypertriglyceridemia who present a risk of pancreatitis and who do not respond adequately to a determined dietary effort to control them.

Limitations of Use

No incremental benefit of NIASPAN coadministered with simvastatin or lovastatin on cardiovascular morbidity and mortality over and above that demonstrated for niacin, simvastatin, or lovastatin monotherapy has been established.

NIASPAN, at doses of 1,500-2,000 mg/day, in combination with simvastatin, did not reduce the incidence of cardiovascular events more than simvastatin in a randomized controlled trial of patients with cardiovascular disease and mean baseline LDL-C levels of 74 mg per deciliter . [see Warnings and Precautions ] (5.1)

2 DOSAGE AND ADMINISTRATION

NIASPAN should be taken at bedtime, after a low-fat snack, and doses should be individualized according to patient response. Therapy with NIASPAN must be initiated at 500 mg at bedtime in order to reduce the incidence and severity of side effects which may occur during early therapy. The recommended dose escalation is shown in below. Table 1

Table 1. Recommended Dosing
 | Week(s) | Daily dose | NIASPAN Dosage
INITIAL TITRATION | 1 to 4 | 500 mg | 1 NIASPAN 500 mg tablet at bedtime
SCHEDULE | 5 to 8 | 1000 mg | 1 NIASPAN 1000 mg tablet or 2 NIASPAN 500 mg tablets at bedtime
 | * | 1500 mg | 2 NIASPAN 750 mg tablets or 3 NIASPAN 500 mg tablets at bedtime
 | * | 2000 mg | 2 NIASPAN 1000 mg tablets or 4 NIASPAN 500 mg tablets at bedtime
* After Week 8, titrate to patient response and tolerance. If response to 1000 mg daily is inadequate, increase dose to 1500 mg daily; may subsequently increase dose to 2000 mg daily. Daily dose should not be increased more than 500 mg in a 4-week period, and doses above 2000 mg daily are not recommended. Women may respond at lower doses than men.

Maintenance Dose

The daily dosage of NIASPAN should not be increased by more than 500 mg in any 4-week period. The recommended maintenance dose is 1000 mg (two 500 mg tablets or one 1000 mg tablet) to 2000 mg (two 1000 mg tablets or four 500 mg tablets) once daily at bedtime. Doses greater than 2000 mg daily are not recommended. Women may respond at lower NIASPAN doses than men . [see Clinical Studies ] (14.2)

Single-dose bioavailability studies have demonstrated that two of the 500 mg and one of the 1000 mg tablet strengths are interchangeable but three of the 500 mg and two of the 750 mg tablet strengths are not interchangeable.

If lipid response to NIASPAN alone is insufficient or if higher doses of NIASPAN are not well tolerated, some patients may benefit from combination therapy with a bile acid binding resin or statin , below and . [see Drug Interactions (7.3) Concomitant Therapy Clinical Studies , ] (14.314.4)

Flushing of the skin may be reduced in frequency or severity by pretreatment with aspirin (up to the recommended dose of 325 mg taken 30 minutes prior to NIASPAN dose). Tolerance to this flushing develops rapidly over the course of several weeks. Flushing, pruritus, and gastrointestinal distress are also greatly reduced by slowly increasing the dose of niacin and avoiding administration on an empty stomach. Concomitant alcoholic, hot drinks or spicy foods may increase the side effects of flushing and pruritus and should be avoided around the time of NIASPAN ingestion. [see Adverse Reactions ] (6.1)

Equivalent doses of NIASPAN should not be substituted for sustained-release (modified-release, timed-release) niacin preparations or immediate-release (crystalline) niacin . Patients previously receiving other niacin products should be started with the recommended NIASPAN titration schedule (see), and the dose should subsequently be individualized based on patient response. [see Warnings and Precautions ] (5) Table 1

If NIASPAN therapy is discontinued for an extended period, reinstitution of therapy should include a titration phase (see). Table 1

NIASPAN tablets should be taken whole and should not be broken, crushed or chewed before swallowing.

Concomitant Therapy

Concomitant Therapy with Lovastatin or Simvastatin

Patients already receiving a stable dose of lovastatin or simvastatin who require further TG-lowering or HDL-raising (e.g., to achieve NCEP non-HDL-C goals), may receive concomitant dosage titration with NIASPAN per NIASPAN recommended initial titration schedule . For patients already receiving a stable dose of NIASPAN who require further LDL-lowering (e.g., to achieve NCEP LDL-C goals), the usual recommended starting dose of lovastatin and simvastatin is 20 mg once a day. Dose adjustments should be made at intervals of 4 weeks or more. Combination therapy with NIASPAN and lovastatin or NIASPAN and simvastatin should not exceed doses of 2000 mg NIASPAN and 40 mg lovastatin or simvastatin daily. [see Dosage and Administration ] (2)

Dosage in Patients with Renal or Hepatic Impairment

Use of NIASPAN in patients with renal or hepatic impairment has not been studied. NIASPAN is contraindicated in patients with significant or unexplained hepatic dysfunction. NIASPAN should be used with caution in patients with renal impairment . [see Warnings and Precautions ] (5)

3 DOSAGE FORMS AND STRENGTHS

- 500 mg unscored, medium-orange, film-coated, capsule-shaped tablets
- 750 mg unscored, medium-orange, film-coated, capsule-shaped tablets
- 1000 mg unscored, medium-orange, film-coated, capsule-shaped tablets

4 CONTRAINDICATIONS

NIASPAN is contraindicated in the following conditions:

- Active liver disease or unexplained persistent elevations in hepatic transaminases [see Warnings and Precautions ] (5.3)
- Patients with active peptic ulcer disease
- Patients with arterial bleeding
- Hypersensitivity to niacin or any component of this medication [see Adverse Reactions ] (6.1)

5 WARNINGS AND PRECAUTIONS

. NIASPAN preparations should not be substituted for equivalent doses of immediate-release (crystalline) niacin. For patients switching from immediate-release niacin to NIASPAN, therapy with NIASPAN should be initiated with low doses (i.e., 500 mg at bedtime) and the NIASPAN dose should then be titrated to the desired therapeutic response [see Dosage and Administration ] (2)

Caution should also be used when NIASPAN is used in patients with unstable angina or in the acute phase of an MI, particularly when such patients are also receiving vasoactive drugs such as nitrates, calcium channel blockers, or adrenergic blocking agents.

Niacin is rapidly metabolized by the liver, and excreted through the kidneys. NIASPAN is contraindicated in patients with significant or unexplained hepatic impairment and should be used with caution in patients with renal impairment. Patients with a past history of jaundice, hepatobiliary disease, or peptic ulcer should be observed closely during NIASPAN therapy. [see Contraindications and Warnings and Precautions ] (4) (5.3)

5.1 Mortality and Coronary Heart Disease Morbidity

The Atherothrombosis Intervention in Metabolic Syndrome with Low HDL/High Triglycerides: Impact on Global Health Outcomes (AIM-HIGH) trial was a randomized placebo-controlled trial of 3414 patients with stable, previously diagnosed cardiovascular disease. Mean baseline lipid levels were LDL-C 74 mg/dL, HDL-C 35 mg/dL, non-HDL-C 111 mg/dL and median triglyceride level of 163-177 mg/dL. Ninety-four percent of patients were on background statin therapy prior to entering the trial. All participants received simvastatin, 40 to 80 mg per day, plus ezetimibe 10 mg per day if needed, to maintain an LDL-C level of 40-80 mg/dL, and were randomized to receive NIASPAN 1500-2000 mg/day (n=1718) or matching placebo (IR Niacin, 100-150 mg, n=1696). On-treatment lipid changes at two years for LDL-C were -12.0% for the simvastatin plus NIASPAN group and -5.5% for the simvastatin plus placebo group. HDL-C increased by 25.0% to 42 mg/dL in the simvastatin plus NIASPAN group and by 9.8% to 38 mg/dL in the simvastatin plus placebo group (P<0.001). Triglyceride levels decreased by 28.6% in the simvastatin plus NIASPAN group and by 8.1% in the simvastatin plus placebo group. The primary outcome was an ITT composite of the first study occurrence of coronary heart disease death, nonfatal myocardial infarction, ischemic stroke, hospitalization for acute coronary syndrome or symptom-driven coronary or cerebral revascularization procedures. The trial was stopped after a mean follow-up period of 3 years owing to a lack of efficacy. The primary outcome occurred in 282 patients in the simvastatin plus NIASPAN group (16.4%) and in 274 patients in the simvastatin plus placebo group (16.2%) (HR 1.02 [95% CI, 0.87-1.21], P=0.79. In an ITT analysis, there were 42 cases of first occurrence of ischemic stroke reported, 27 (1.6%) in the simvastatin plus NIASPAN group and 15 (0.9%) in the simvastatin plus placebo group, a non-statistically significant (HR 1.79, [95%CI = 0.95-3.36], p=0.071). The on-treatment ischemic stroke events were 19 for the simvastatin plus NIASPAN group and 15 for the simvastatin plus placebo group . result [see Adverse Reactions ] (6.1)

5.2 Skeletal Muscle

Cases of rhabdomyolysis have been associated with concomitant administration of lipid-altering doses (≥1 g/day) of niacin and statins. Physicians contemplating combined therapy with statins and NIASPAN should carefully weigh the potential benefits and risks and should carefully monitor patients for any signs and symptoms of muscle pain, tenderness, or weakness, particularly during the initial months of therapy and during any periods of upward dosage titration of either drug. Periodic serum creatine phosphokinase (CPK) and potassium determinations should be considered in such situations, but there is no assurance that such monitoring will prevent the occurrence of severe myopathy.

The risk for myopathy and rhabdomyolysis are increased when lovastatin or simvastatin are coadministered with NIASPAN, particularly in elderly patients and patients with diabetes, renal failure, or uncontrolled hypothyroidism.

5.3 Liver Dysfunction

Cases of severe hepatic toxicity, including fulminant hepatic necrosis, have occurred in patients who have substituted sustained-release (modified-release, timed-release) niacin products for immediate-release (crystalline) niacin at equivalent doses.

NIASPAN should be used with caution in patients who consume substantial quantities of alcohol and/or have a past history of liver disease. Active liver diseases or unexplained transaminase elevations are contraindications to the use of NIASPAN.

Niacin preparations have been associated with abnormal liver tests. In three placebo-controlled clinical trials involving titration to final daily NIASPAN doses ranging from 500 to 3000 mg, 245 patients received NIASPAN for a mean duration of 17 weeks. No patient with normal serum transaminase levels (AST, ALT) at baseline experienced elevations to more than 3 times the upper limit of normal (ULN) during treatment with NIASPAN. In these studies, fewer than 1% (2/245) of NIASPAN patients discontinued due to transaminase elevations greater than 2 times the ULN.

In three safety and efficacy studies with a combination tablet of NIASPAN and lovastatin involving titration to final daily doses (expressed as mg of niacin/ mg of lovastatin) 500 mg/10 mg to 2500 mg/40 mg, ten of 1028 patients (1.0%) experienced reversible elevations in AST/ALT to more than 3 times the ULN. Three of ten elevations occurred at doses outside the recommended dosing limit of 2000 mg/40 mg; no patient receiving 1000 mg/20 mg had 3-fold elevations in AST/ALT.

Niacin extended-release and simvastatin can cause abnormal liver tests. In a simvastatin-controlled, 24 week study with a fixed dose combination of NIASPAN and simvastatin in 641 patients, there were no persistent increases (more than 3x the ULN) in serum transaminases. In three placebo-controlled clinical studies of extended-release niacin there were no patients with normal serum transaminase levels at baseline who experienced elevations to more than 3x the ULN. Persistent increases (more than 3x the ULN) in serum transaminases have occurred in approximately 1% of patients who received simvastatin in clinical studies. When drug treatment was interrupted or discontinued in these patients, the transaminases levels usually fell slowly to pretreatment levels. The increases were not associated with jaundice or other clinical signs or symptoms. There was no evidence of hypersensitivity.

In the placebo-controlled clinical trials and the long-term extension study, elevations in transaminases did not appear to be related to treatment duration; elevations in AST levels did appear to be dose related. Transaminase elevations were reversible upon discontinuation of NIASPAN.

Liver function tests should be performed on all patients during therapy with NIASPAN. Serum transaminase levels, including AST and ALT (SGOT and SGPT), should be monitored before treatment begins, every 6 to 12 weeks for the first year, and periodically thereafter (e.g., at approximately 6-month intervals). Special attention should be paid to patients who develop elevated serum transaminase levels, and in these patients, measurements should be repeated promptly and then performed more frequently. If the transaminase levels show evidence of progression, particularly if they rise to 3 times ULN and are persistent, or if they are associated with symptoms of nausea, fever, and/or malaise, the drug should be discontinued.

5.4 Laboratory Abnormalities

Niacin treatment can increase fasting blood glucose. Frequent monitoring of blood glucose should be performed to ascertain that the drug is producing no adverse effects. Diabetic patients may experience a dose-related increase in glucose intolerance. Diabetic or potentially diabetic patients should be observed closely during treatment with NIASPAN, particularly during the first few months of use or dose adjustment; adjustment of diet and/or hypoglycemic therapy may be necessary. Increase in Blood Glucose:

NIASPAN has been associated with small but statistically significant dose-related reductions in platelet count (mean of -11% with 2000 mg). Caution should be observed when NIASPAN is administered concomitantly with anticoagulants; platelet counts should be monitored closely in such patients. Reduction in platelet count:

NIASPAN has been associated with small but statistically significant increases in prothrombin time (mean of approximately +4%); accordingly, patients undergoing surgery should be carefully evaluated. Caution should be observed when NIASPAN is administered concomitantly with anticoagulants; prothrombin time should be monitored closely in such patients. Increase in Prothrombin Time (PT):

Elevated uric acid levels have occurred with niacin therapy, therefore use with caution in patients predisposed to gout. Increase in Uric Acid:

In placebo-controlled trials, NIASPAN has been associated with small but statistically significant, dose-related reductions in phosphorus levels (mean of -13% with 2000 mg). Although these reductions were transient, phosphorus levels should be monitored periodically in patients at risk for hypophosphatemia. Decrease in Phosphorus:

6 ADVERSE REACTIONS

Because clinical studies are conducted under widely varying conditions, adverse reaction rates observed in the clinical studies of a drug cannot be directly compared to rates in the clinical studies of another drug and may not reflect the rates observed in practice.

6.1 Clinical Studies Experience

In the placebo-controlled clinical trials database of 402 patients (age range 21-75 years, 33% women, 89% Caucasians, 7% Blacks, 3% Hispanics, 1% Asians) with a median treatment duration of 16 weeks, 16% of patients on NIASPAN and 4% of patients on placebo discontinued due to adverse reactions. The most common adverse reactions in the group of patients treated with NIASPAN that led to treatment discontinuation and occurred at a rate greater than placebo were flushing (6% vs. 0%), rash (2% vs. 0%), diarrhea (2% vs. 0%), nausea (1% vs. 0%), and vomiting (1% vs. 0%). The most commonly reported adverse reactions (incidence >5% and greater than placebo) in the NIASPAN controlled clinical trial database of 402 patients were flushing, diarrhea, nausea, vomiting, increased cough and pruritus.

In the placebo-controlled clinical trials, flushing episodes (i.e., warmth, redness, itching and/or tingling) were the most common treatment-emergent adverse reactions (reported by as many as 88% of patients) for NIASPAN. Spontaneous reports suggest that flushing may also be accompanied by symptoms of dizziness, tachycardia, palpitations, shortness of breath, sweating, burning sensation/skin burning sensation, chills, and/or edema, which in rare cases may lead to syncope. In pivotal studies, 6% (14/245) of NIASPAN patients discontinued due to flushing. In comparisons of immediate-release (IR) niacin and NIASPAN, although the proportion of patients who flushed was similar, fewer flushing episodes were reported by patients who received NIASPAN. Following 4 weeks of maintenance therapy at daily doses of 1500 mg, the incidence of flushing over the 4-week period averaged 8.6 events per patient for IR niacin versus 1.9 following NIASPAN.

Other adverse reactions occurring in ≥5% of patients treated with NIASPAN and at an incidence greater than placebo are shown in below. Table 2

Table 2. Treatment-Emergent Adverse Reactions by Dose Level in ≥ 5% of Patients and at an Incidence Greater than Placebo; Regardless of Causality Assessment in Placebo-Controlled Clinical Trials
 | Placebo-Controlled Studies NIASPAN Treatment @
 |  |  | Recommended Daily Maintenance Doses †
 | Placebo | 500 mg‡ | 1000 mg | 1500 mg | 2000 mg
 | (n = 157) | (n = 87) | (n = 110) | (n = 136) | (n = 95)
 | % | % | % | % | %
Gastrointestinal Disorders
Diarrhea | 13 | 7 | 10 | 10 | 14
Nausea | 7 | 5 | 6 | 4 | 11
Vomiting | 4 | 0 | 2 | 4 | 9
Respiratory
Cough, Increased | 6 | 3 | 2 | < 2 | 8
Skin and Subcutaneous Tissue Disorders
Pruritus | 2 | 8 | 0 | 3 | 0
Rash | 0 | 5 | 5 | 5 | 0
Vascular Disorders
Flushing& | 19 | 68 | 69 | 63 | 55
Note: Percentages are calculated from the total number of patients in each column. Adverse reactions are reported at the initial dose where they occur. Pooled results from placebo-controlled studies; for NIASPAN, n = 245 and median treatment duration = 16 weeks. Number of NIASPAN patients (n) are not additive across doses. The 500 mg/day dose is outside the recommended daily maintenance dosing range . 10 patients discontinued before receiving 500 mg, therefore they were not included.
†
@
‡[see Dosage and Administration ] (2)
&

In general, the incidence of adverse events was higher in women compared to men.

Atherothrombosis Intervention in Metabolic Syndrome with Low HDL/High Triglycerides: Impact on Global Health Outcomes (AIM-HIGH)

In AIM-HIGH involving 3414 patients (mean age of 64 years, 15% women, 92% Caucasians, 34% with diabetes mellitus) with stable, previously diagnosed cardiovascular disease, all patients received simvastatin, 40 to 80 mg per day, plus ezetimibe 10 mg per day if needed, to maintain an LDL-C level of 40-80 mg/dL, and were randomized to receive NIASPAN 1500-2000 mg/day (n=1718) or matching placebo (IR Niacin, 100-150 mg, n=1696). The incidence of the adverse reactions of “blood glucose increased” (6.4% vs. 4.5%) and “diabetes mellitus” (3.6% vs. 2.2%) was significantly higher in the simvastatin plus NIASPAN group as compared to the simvastatin plus placebo group. There were 5 cases of rhabdomyolysis reported, 4 (0.2%) in the simvastatin plus NIASPAN group and one (<0.1%) in the simvastatin plus placebo group . [see Warnings and Precautions ] (5.1)

6.2 Postmarketing Experience

Because the below reactions are reported voluntarily from a population of uncertain size, it is generally not possible to reliably estimate their frequency or establish a causal relationship to drug exposure.

The following additional adverse reactions have been identified during post-approval use of NIASPAN:

Hypersensitivity reactions, including anaphylaxis, angioedema, urticaria, flushing, dyspnea, tongue edema, larynx edema, face edema, peripheral edema, laryngismus, and vesiculobullous rash; maculopapular rash; dry skin; tachycardia; palpitations; atrial fibrillation; other cardiac arrhythmias; syncope; hypotension; postural hypotension; blurred vision; macular edema; peptic ulcers; eructation; flatulence; hepatitis; jaundice; decreased glucose tolerance; gout; myalgia; myopathy; dizziness; insomnia; asthenia; nervousness; paresthesia; dyspnea; sweating; burning sensation/skin burning sensation; skin discoloration, and migraine.

Clinical Laboratory Abnormalities

Elevations in serum transaminases , LDH, fasting glucose, uric acid, total bilirubin, amylase and creatine kinase, and reduction in phosphorus. Chemistry:[see Warnings and Precautions ] (5.3)

Slight reductions in platelet counts and prolongation in prothrombin time . Hematology:[see Warnings and Precautions ] (5.4)

7 DRUG INTERACTIONS

7.1 Statins

Caution should be used when prescribing niacin (≥1 gm/day) with statins as these drugs can increase risk of myopathy/rhabdomyolysis. Combination therapy with NIASPAN and lovastatin or NIASPAN and simvastatin should not exceed doses of 2000 mg NIASPAN and 40 mg lovastatin or simvastatin daily. . [see Warnings and Precautions and Clinical Pharmacology ] (5) (12.3)

7.2 Bile Acid Sequestrants

An study results suggest that the bile acid-binding resins have high niacin binding capacity. Therefore, 4 to 6 hours, or as great an interval as possible, should elapse between the ingestion of bile acid-binding resins and the administration of NIASPAN . in vitro [see Clinical Pharmacology ] (12.3)

7.3 Aspirin

Concomitant aspirin may decrease the metabolic clearance of nicotinic acid. The clinical relevance of this finding is unclear.

7.4 Antihypertensive Therapy

Niacin may potentiate the effects of ganglionic blocking agents and vasoactive drugs resulting in postural hypotension.

7.5 Other

Vitamins or other nutritional supplements containing large doses of niacin or related compounds such as nicotinamide may potentiate the adverse effects of NIASPAN.

7.6 Laboratory Test Interactions

Niacin may produce false elevations in some fluorometric determinations of plasma or urinary catecholamines. Niacin may also give false-positive reactions with cupric sulfate solution (Benedict’s reagent) in urine glucose tests.

8 USE IN SPECIFIC POPULATIONS

8.1 Pregnancy

Pregnancy Category C.

Animal reproduction studies have not been conducted with niacin or with NIASPAN. It is also not known whether niacin at doses typically used for lipid disorders can cause fetal harm when administered to pregnant women or whether it can affect reproductive capacity. If a woman receiving niacin for primary hyperlipidemia becomes pregnant, the drug should be discontinued. If a woman being treated with niacin for hypertriglyceridemia conceives, the benefits and risks of continued therapy should be assessed on an individual basis.

All statins are contraindicated in pregnant and nursing women. When NIASPAN is administered with a statin in a woman of childbearing potential, refer to the pregnancy category and product labeling for the statin.

8.3 Nursing Mothers

Niacin is excreted into human milk but the actual infant dose or infant dose as a percent of the maternal dose is not known. Because of the potential for serious adverse reactions in nursing infants from lipid-altering doses of nicotinic acid, a decision should be made whether to discontinue nursing or to discontinue the drug, taking into account the importance of the drug to the mother. No studies have been conducted with NIASPAN in nursing mothers.

8.4 Pediatric Use

Safety and effectiveness of niacin therapy in pediatric patients (≤16 years) have not been established.

8.5 Geriatric Use

Of 979 patients in clinical studies of NIASPAN, 21% of the patients were age 65 and over. No overall differences in safety and effectiveness were observed between these patients and younger patients, and other reported clinical experience has not identified differences in responses between the elderly and younger patients, but greater sensitivity of some older individuals cannot be ruled out.

8.6 Renal Impairment

No studies have been performed in this population. NIASPAN should be used with caution in patients with renal impairment . [see Warnings and Precautions ] (5)

8.7 Hepatic Impairment

No studies have been performed in this population. NIASPAN should be used with caution in patients with a past history of liver disease and/or who consume substantial quantities of alcohol. Active liver disease, unexplained transaminase elevations and significant or unexplained hepatic dysfunction are contraindications to the use of NIASPAN . [see Contraindications and Warnings and Precautions ] (4.0) (5.3)

8.8 Gender

Data from the clinical trials suggest that women have a greater hypolipidemic response than men at equivalent doses of NIASPAN.

10 OVERDOSAGE

Supportive measures should be undertaken in the event of an overdose.

11 DESCRIPTION

NIASPAN (niacin tablet, film-coated extended-release), contains niacin, which at therapeutic doses is an antihyperlipidemic agent. Niacin (nicotinic acid, or 3-pyridinecarboxylic acid) is a white, crystalline powder, very soluble in water, with the following structural formula:

NIASPAN is an unscored, medium-orange, film-coated tablet for oral administration and is available in three tablet strengths containing 500, 750, and 1000 mg niacin. NIASPAN tablets also contain the inactive ingredients hypromellose, povidone, stearic acid, and polyethylene glycol, and the following coloring agents: FD&C yellow #6/sunset yellow FCF Aluminum Lake, synthetic red and yellow iron oxides, and titanium dioxide.

12 CLINICAL PHARMACOLOGY

12.1 Mechanism of Action

The mechanism by which niacin alters lipid profiles has not been well defined. It may involve several actions including partial inhibition of release of free fatty acids from adipose tissue, and increased lipoprotein lipase activity, which may increase the rate of chylomicron triglyceride removal from plasma. Niacin decreases the rate of hepatic synthesis of VLDL and LDL, and does not appear to affect fecal excretion of fats, sterols, or bile acids.

12.2 Pharmacodynamics

Niacin functions in the body after conversion to nicotinamide adenine dinucleotide (NAD) in the NAD coenzyme system. Niacin (but not nicotinamide) in gram doses reduces total cholesterol (TC), low density lipoprotein cholesterol (LDL-C), and triglycerides (TG), and increases high-density lipoprotein cholesterol (HDL-C). The magnitude of individual lipid and lipoprotein responses may be influenced by the severity and type of underlying lipid abnormality. The increase in HDL-C is associated with an increase in apolipoprotein A-I (Apo A-I) and a shift in the distribution of HDL subfractions. These shifts include an increase in the HDL :HDL ratio, and an elevation in lipoprotein A-I (Lp A-I, an HDL-C particle containing only Apo A-I). Niacin treatment also decreases serum levels of apolipoprotein B-100 (Apo B), the major protein component of the very low-density lipoprotein (VLDL) and LDL fractions, and of Lp(a), a variant form of LDL independently associated with coronary risk. In addition, preliminary reports suggest that niacin causes favorable LDL particle size transformations, although the clinical relevance of this effect requires further investigation. The effect of niacin-induced changes in lipids/proteins on cardiovascular morbidity or mortality in individuals without preexisting coronary disease has not been established.23

A variety of clinical studies have demonstrated that elevated levels of TC, LDL-C, and Apo B promote human atherosclerosis. Similarly, decreased levels of HDL-C are associated with the development of atherosclerosis. Epidemiological investigations have established that cardiovascular morbidity and mortality vary directly with the level of Total-C and LDL-C, and inversely with the level of HDL-C.

Like LDL, cholesterol-enriched triglyceride-rich lipoproteins, including VLDL, intermediate-density lipoprotein (IDL), and their remnants, can also promote atherosclerosis. Elevated plasma TG are frequently found in a triad with low HDL-C levels and small LDL particles, as well as in association with non-lipid metabolic risk factors for coronary heart disease (CHD). As such, total plasma TG has not consistently been shown to be an independent risk factor for CHD. Furthermore, the independent effect of raising HDL-C or lowering TG on the risk of coronary and cardiovascular morbidity and mortality has not been determined.

12.3 Pharmacokinetics

Absorption

Due to extensive and saturable first-pass metabolism, niacin concentrations in the general circulation are dose dependent and highly variable. Time to reach the maximum niacin plasma concentrations was about 5 hours following NIASPAN. To reduce the risk of gastrointestinal (GI) upset, administration of NIASPAN with a low-fat meal or snack is recommended.

Single-dose bioavailability studies have demonstrated that the 500 mg and 1000 mg tablet strengths are dosage form equivalent but the 500 mg and 750 mg tablet strengths are not dosage form equivalent.

Metabolism

The pharmacokinetic profile of niacin is complicated due to extensive first-pass metabolism that is dose-rate specific and, at the doses used to treat dyslipidemia, saturable. In humans, one pathway is through a simple conjugation step with glycine to form nicotinuric acid (NUA). NUA is then excreted in the urine, although there may be a small amount of reversible metabolism back to niacin. The other pathway results in the formation of nicotinamide adenine dinucleotide (NAD). It is unclear whether nicotinamide is formed as a precursor to, or following the synthesis of, NAD. Nicotinamide is further metabolized to at least N-methylnicotinamide (MNA) and nicotinamide-N-oxide (NNO). MNA is further metabolized to two other compounds, N-methyl-2-pyridone-5-carboxamide (2PY) and N-methyl-4-pyridone-5-carboxamide (4PY). The formation of 2PY appears to predominate over 4PY in humans. At the doses used to treat hyperlipidemia, these metabolic pathways are saturable, which explains the nonlinear relationship between niacin dose and plasma concentrations following multiple-dose NIASPAN administration.

Nicotinamide does not have hypolipidemic activity; the activity of the other metabolites is unknown.

Elimination

Following single and multiple doses, approximately 60 to 76% of the niacin dose administered as NIASPAN was recovered in urine as niacin and metabolites; up to 12% was recovered as unchanged niacin after multiple dosing. The ratio of metabolites recovered in the urine was dependent on the dose administered.

Pediatric Use

No pharmacokinetic studies have been performed in this population (≤16 years) . [see Use in Specific Populations ] (8.4)

Geriatric Use

No pharmacokinetic studies have been performed in this population (> 65 years) . [see Use in Specific Populations ] (8.5)

Renal Impairment

No pharmacokinetic studies have been performed in this population. NIASPAN should be used with caution in patients with renal disease . [see Warnings and Precautions ] (5)

Hepatic Impairment

No pharmacokinetic studies have been performed in this population. Active liver disease, unexplained transaminase elevations and significant or unexplained hepatic dysfunction are contraindications to the use of NIASPAN . [see Contraindications and Warnings and Precautions ] (4) (5.3)

Gender

Steady-state plasma concentrations of niacin and metabolites after administration of NIASPAN are generally higher in women than in men, with the magnitude of the difference varying with dose and metabolite. This gender differences observed in plasma levels of niacin and its metabolites may be due to gender-specific differences in metabolic rate or volume of distribution. Recovery of niacin and metabolites in urine, however, is generally similar for men and women, indicating that absorption is similar for both genders . [see Gender ] (8.8)

Drug interactions

Fluvastatin

Niacin did not affect fluvastatin pharmacokinetics . [see Drug Interactions ] (7.1)

Lovastatin

When NIASPAN 2000 mg and lovastatin 40 mg were co-administered, NIASPAN increased lovastatin C and AUC by 2% and 14%, respectively, and decreased lovastatin acid C and AUC by 22% and 2%, respectively. Lovastatin reduced NIASPAN bioavailability by 2-3% .maxmax [see Drug Interactions ] (7.1)

Simvastatin

When NIASPAN 2000 mg and simvastatin 40 mg were co-administered, NIASPAN increased simvastatin C and AUC by 1% and 9%, respectively, and simvastatin acid C and AUC by 2% and 18%, respectively. Simvastatin reduced NIASPAN bioavailability by 2% .maxmax [see Drug Interactions ] (7.1)

Bile Acid Sequestrants

An study was carried out investigating the niacin-binding capacity of colestipol and cholestyramine. About 98% of available niacin was bound to colestipol, with 10 to 30% binding to cholestyramine . in vitro [see Drug Interactions ] (7.2)

13 NONCLINICAL TOXICOLOGY

13.1 Carcinogenesis and Mutagenesis and Impairment of Fertility

Niacin administered to mice for a lifetime as a 1% solution in drinking water was not carcinogenic. The mice in this study received approximately 6 to 8 times a human dose of 3000 mg/day as determined on a mg/m basis. Niacin was negative for mutagenicity in the Ames test. No studies on impairment of fertility have been performed. No studies have been conducted with NIASPAN regarding carcinogenesis, mutagenesis, or impairment of fertility.^2

14 CLINICAL STUDIES

14.1 Niacin Clinical Studies

The role of LDL-C in atherogenesis is supported by pathological observations, clinical studies, and many animal experiments. Observational epidemiological studies have clearly established that high TC or LDL-C and low HDL-C are risk factors for CHD. Additionally, elevated levels of Lp(a) have been shown to be independently associated with CHD risk.

Niacin’s ability to reduce mortality and the risk of definite, nonfatal myocardial infarction (MI) has been assessed in long-term studies. The Coronary Drug Project, completed in 1975, was designed to assess the safety and efficacy of niacin and other lipid-altering drugs in men 30 to 64 years old with a history of MI. Over an observation period of 5 years, niacin treatment was associated with a statistically significant reduction in nonfatal, recurrent MI. The incidence of definite, nonfatal MI was 8.9% for the 1,119 patients randomized to nicotinic acid versus 12.2% for the 2,789 patients who received placebo (<0.004). Total mortality was similar in the two groups at 5 years (24.4% with nicotinic acid versus 25.4% with placebo; =N.S.). At the time of a 15-year follow-up, there were 11% (69) fewer deaths in the niacin group compared to the placebo cohort (52.0% versus 58.2%; =0.0004). However, mortality at 15 years was not an original endpoint of the Coronary Drug Project. In addition, patients had not received niacin for approximately 9 years, and confounding variables such as concomitant medication use and medical or surgical treatments were not controlled. ppp

The Cholesterol-Lowering Atherosclerosis Study (CLAS) was a randomized, placebo-controlled, angiographic trial testing combined colestipol and niacin therapy in 162 non-smoking males with previous coronary bypass surgery. The primary, per-subject cardiac endpoint was global coronary artery change score. After 2 years, 61% of patients in the placebo cohort showed disease progression by global change score (n=82), compared with only 38.8% of drug-treated subjects (n=80), when both native arteries and grafts were considered (<0.005); disease regression also occurred more frequently in the drug-treated group (16.2% versus 2.4%; =0.002). In a follow-up to this trial in a subgroup of 103 patients treated for 4 years, again, significantly fewer patients in the drug-treated group demonstrated progression than in the placebo cohort (48% versus 85%, respectively; <0.0001). ppp

The Familial Atherosclerosis Treatment Study (FATS) in 146 men ages 62 and younger with Apo B levels ≥125 mg/dL, established coronary artery disease, and family histories of vascular disease, assessed change in severity of disease in the proximal coronary arteries by quantitative arteriography. Patients were given dietary counseling and randomized to treatment with either conventional therapy with double placebo (or placebo plus colestipol if the LDL-C was elevated); lovastatin plus colestipol; or niacin plus colestipol. In the conventional therapy group, 46% of patients had disease progression (and no regression) in at least one of nine proximal coronary segments; regression was the only change in 11%. In contrast, progression (as the only change) was seen in only 25% in the niacin plus colestipol group, while regression was observed in 39%. Though not an original endpoint of the trial, clinical events (death, MI, or revascularization for worsening angina) occurred in 10 of 52 patients who received conventional therapy, compared with 2 of 48 who received niacin plus colestipol.

The Harvard Atherosclerosis Reversibility Project (HARP) was a randomized placebo-controlled, 2.5-year study of the effect of a stepped-care antihyperlipidemic drug regimen on 91 patients (80 men and 11 women) with CHD and average baseline TC levels less than 250 mg/dL and ratios of TC to HDL-C greater than 4.0. Drug treatment consisted of an HMG-CoA reductase inhibitor administered alone as initial therapy followed by addition of varying dosages of either a slow-release nicotinic acid, cholestyramine, or gemfibrozil. Addition of nicotinic acid to the HMG-CoA reductase inhibitor resulted in further statistically significant mean reductions in TC, LDL-C, and TG, as well as a further increase in HDL-C in a majority of patients (40 of 44 patients). The ratios of TC to HDL-C and LDL-C to HDL-C were also significantly reduced by this combination drug regimen . [see Warnings and Precautions ] (5.2)

14.2 NIASPAN Clinical Studies

In two randomized, double-blind, parallel, multi-center, placebo-controlled trials, NIASPAN dosed at 1000, 1500 or 2000 mg daily at bedtime with a low-fat snack for 16 weeks (including 4 weeks of dose escalation) favorably altered lipid profiles compared to placebo (). Women appeared to have a greater response than men at each NIASPAN dose level (see , below). Placebo-Controlled Clinical Studies in Patients with Primary Hyperlipidemia and Mixed Dyslipidemia: Table 3 Gender Effect

Table 3. Lipid Response to NIASPAN Therapy
 |  | Mean Percent Change from Baseline to Week 16*
Treatment | n | TC | LDL-C | HDL-C | TC/HDL-C | TG | Lp(a) | Apo B | Apo A-I
NIASPAN 1000 mg at bedtime | 41 | -3 | -5 | +18 | -17 | -21 | -13 | -6 | +9
NIASPAN 2000 mg at bedtime | 41 | -10 | -14 | +22 | -25 | -28 | -27 | -16 | +8
Placebo | 40 | 0 | -1 | +4 | -3 | 0 | 0 | +1 | +3
NIASPAN 1500 mg at bedtime | 76 | -8 | -12 | +20 | -20 | -13 | -15 | -12 | +8
Placebo | 73 | +2 | +1 | +2 | +1 | +12 | +2 | +1 | +2
n = number of patients at baseline; * Mean percent change from baseline for all NIASPAN doses was significantly different (< 0.05) from placebo for all lipid parameters shown except Apo A-I at 2000 mg.
p

In a double-blind, multi-center, forced dose-escalation study, monthly 500 mg increases in NIASPAN dose resulted in incremental reductions of approximately 5% in LDL-C and Apo B levels in the daily dose range of 500 mg through 2000 mg (). Women again tended to have a greater response to NIASPAN than men (see , below). Table 4 Gender Effect

Table 4. Lipid Response in Dose-Escalation Study
 |  | Mean Percent Change from Baseline*
Treatment | n | TC | LDL-C | HDL-C | TC/HDL-C | TG | Lp(a) | Apo B | Apo A-I
Placebo‡ | 44 | -2 | -1 | +5 | -7 | -6 | -5 | -2 | +4
NIASPAN | 87
500 mg at bedtime |  | -2 | -3 | +10 | -10 | -5 | -3 | -2 | +5
1000 mg at bedtime |  | -5 | -9 | +15 | -17 | -11 | -12 | -7 | +8
1500 mg at bedtime |  | -11 | -14 | +22 | -26 | -28 | -20 | -15 | +10
2000 mg at bedtime |  | -12 | -17 | +26 | -29 | -35 | -24 | -16 | +12
n = number of patients enrolled; Placebo data shown are after 24 weeks of placebo treatment. * For all NIASPAN doses except 500 mg, mean percent change from baseline was significantly different (< 0.05) from placebo for all lipid parameters shown except Lp(a) and Apo A-I which were significantly different from placebo starting with 1500 mg and 2000 mg, respectively.
‡
p

Pooled results for major lipids from these three placebo-controlled studies are shown below (). Table 5

Table 5. Selected Lipid Response to NIASPAN in Placebo-Controlled Clinical Studies*
 | Mean Baseline and Median Percent Change from Baseline (25 , 75 Percentiles) thth
NIASPAN Dose | n | LDL-C | HDL-C | TG
1000 mg at bedtime | 104
Baseline (mg/dL) |  | 218 | 45 | 172
Percent Change |  | -7 (-15, 0) | +14 (+7, +23) | -16 (-34, +3)
1500 mg at bedtime | 120
Baseline (mg/dL) |  | 212 | 46 | 171
Percent Change |  | -13 (-21, -4) | +19 (+9, +31) | -25 (-45, -2)
2000 mg at bedtime | 85
Baseline (mg/dL) |  | 220 | 44 | 160
Percent Change |  | -16 (-26, -7) | +22 (+15, +34) | -38 (-52, -14)
* Represents pooled analyses of results; minimum duration on therapy at each dose was 4 weeks.

Combined data from the three placebo-controlled NIASPAN studies in patients with primary hyperlipidemia and mixed dyslipidemia suggest that, at each NIASPAN dose level studied, changes in lipid concentrations are greater for women than for men (). Gender Effect: Table 6

Table 6. Effect of Gender on NIASPAN Dose Response
 |  | Mean Percent Change from Baseline
NIASPAN | n | LDL-C |  | HDL-C |  | TG |  | Apo B
Dose | (M/F) | M | F | M | F | M | F | M | F
500 mg at bedtime | 50/37 | -2 | -5 | +11 | +8 | -3 | -9 | -1 | -5
1000 mg at bedtime | 76/52 | -6* | -11* | +14 | +20 | -10 | -20 | -5* | -10*
1500 mg at bedtime | 104/59 | -12 | -16 | +19 | +24 | -17 | -28 | -13 | -15
2000 mg at bedtime | 75/53 | -15 | -18 | +23 | +26 | -30 | -36 | -16 | -16
n = number of male/female patients enrolled. * Percent change significantly different between genders (< 0.05).
p

In a double-blind, multi-center, 19-week study the lipid-altering effects of NIASPAN (forced titration to 2000 mg at bedtime) were compared to baseline in patients whose primary lipid abnormality was a low level of HDL-C (HDL-C ≤40 mg/dL, TG ≤400 mg/dL, and LDL-C ≤160, or <130 mg/dL in the presence of CHD). Results are shown below (). Other Patient Populations: Table 7

Table 7. Lipid Response to NIASPAN in Patients with Low HDL-C
 |  |  | Mean Baseline and Mean Percent Change from Baseline*
 | n | TC | LDL-C | HDL-C | TC/HDL-C | TG | Lp(a)† | Apo B† | Apo A-I† | Lp A-I††
Baseline (mg/dL) | 88 | 190 | 120 | 31 | 6 | 194 | 8 | 106 | 105 | 32
Week 19 (% Change) | 71 | -3 | 0 | +26 | -22 | -30 | -20 | -9 | +11 | +20
n = number of patients * Mean percent change from baseline was significantly different (< 0.05) for all lipid parameters shown except LDL-C. n = 72 at baseline and 69 at week 19. n = 30 at baseline and week 19.
p
†
††

At NIASPAN 2000 mg/day, median changes from baseline (25th, 75th percentiles) for LDL-C, HDL-C, and TG were -3% (-14, +12%), +27% (+13, +38%), and -33% (-50, -19%), respectively.

14.3 NIASPAN and Lovastatin Clinical Studies

Combination NIASPAN and Lovastatin Study: In a multi-center, randomized, double-blind, parallel, 28-week study, a combination tablet of NIASPAN and lovastatin was compared to each individual component in patients with Type IIa and IIb hyperlipidemia. Using a forced dose-escalation study design, patients received each dose for at least 4 weeks. Patients randomized to treatment with the combination tablet of NIASPAN and lovastatin initially received 500 mg/20 mg (expressed as mg of niacin/mg of lovastatin) once daily before bedtime. The dose was increased by 500 mg at 4-week intervals (based on the NIASPAN component) to a maximum dose of 1000 mg/20 mg in one-half of the patients and 2000 mg/40 mg in the other half. The NIASPAN monotherapy group underwent a similar titration from 500 mg to 2000 mg. The patients randomized to lovastatin monotherapy received 20 mg for 12 weeks titrated to 40 mg for up to 16 weeks. Up to a third of the patients randomized to the combination tablet of NIASPAN and lovastatin or NIASPAN monotherapy discontinued prior to Week 28. Results from this study showed that combination therapy decreased LDL-C, TG and Lp(a), and increased HDL-C in a dose-dependent fashion (Tables 8, 9, 10, and 11). Results from this study for LDL-C mean percent change from baseline (the primary efficacy variable) showed that:

1. LDL-lowering with the combination tablet of NIASPAN and lovastatin was significantly greater than that achieved with lovastatin 40 mg only after 28 weeks of titration to a dose of 2000 mg/40 mg (<0.0001) p
2. The combination tablet of NIASPAN and lovastatin at doses of 1000 mg/20 mg or higher achieved greater LDL-lowering than NIASPAN (<0.0001) p

The LDL-C results are summarized in . Table 8

Table 8. LDL-C mean percent change from baseline
Week | Combination Tablet of NIASPAN and Lovastatin |  |  | NIASPAN |  |  | Lovastatin
 | n* | Dose | LDL | n* | Dose | LDL | n* | Dose | LDL
 |  | (mg/mg) |  |  | (mg) |  |  | (mg)
Baseline | 57 | – | 190.9 mg/dL | 61 | – | 189.7 mg/dL | 61 | – | 185.6 mg/dL
12 | 47 | 1000/20 | -30% | 46 | 1000 | -3% | 56 | 20 | -29%
16 | 45 | 1000/40 | -36% | 44 | 1000 | -6% | 56 | 40 | -31%
20 | 42 | 1500/40 | -37% | 43 | 1500 | -12% | 54 | 40 | -34%
28 | 42 | 2000/40 | -42% | 41 | 2000 | -14% | 53 | 40 | -32%
* n = number of patients remaining in trial at each time point

Combination therapy achieved significantly greater HDL-raising compared to lovastatin and NIASPAN monotherapy at all doses (). Table 9

Table 9. HDL-C mean percent change from baseline
Week | Combination Tablet of NIASPAN and Lovastatin |  |  | NIASPAN |  |  | Lovastatin
 | n* | Dose | HDL | n* | Dose | HDL | n* | Dose | HDL
 |  | (mg/mg) |  |  | (mg) |  |  | (mg)
Baseline | 57 | – | 45 mg/dL | 61 | – | 47 mg/dL | 61 | – | 43 mg/dL
12 | 47 | 1000/20 | +20% | 46 | 1000 | +14% | 56 | 20 | +3%
16 | 45 | 1000/40 | +20% | 44 | 1000 | +15% | 56 | 40 | +5%
20 | 42 | 1500/40 | +27% | 43 | 1500 | +22% | 54 | 40 | +6%
28 | 42 | 2000/40 | +30% | 41 | 2000 | +24% | 53 | 40 | +6%
* n = number of patients remaining in trial at each time point

In addition, combination therapy achieved significantly greater TG lowering at doses of 1000 mg/20mg or greater compared to lovastatin and NIASPAN monotherapy (). Table 10

Table 10. TG median percent change from baseline
Week | Combination Tablet of NIASPAN and Lovastatin |  |  | NIASPAN |  |  | Lovastatin
 | n* | Dose | TG | n* | Dose | TG | n* | Dose | TG
 |  | (mg/mg) |  |  | (mg) |  |  | (mg)
Baseline | 57 | – | 174 mg/dL | 61 | – | 186 mg/dL | 61 | – | 171 mg/dL
12 | 47 | 1000/20 | -32% | 46 | 1000 | -22% | 56 | 20 | -20%
16 | 45 | 1000/40 | -39% | 44 | 1000 | -23% | 56 | 40 | -17%
20 | 42 | 1500/40 | -44% | 43 | 1500 | -31% | 54 | 40 | -21%
28 | 42 | 2000/40 | -44% | 41 | 2000 | -31% | 53 | 40 | -20%
* n = number of patients remaining in trial at each time point

The Lp(a)-lowering effects of combination therapy and NIASPAN monotherapy were similar, and both were superior to lovastatin (). The independent effect of lowering Lp(a) with NIASPAN or combination therapy on the risk of coronary and cardiovascular morbidity and mortality has not been determined. Table 11

Table 11. Lp(a) median percent change from baseline
Week | Combination Tablet of NIASPAN and Lovastatin |  |  | NIASPAN |  |  | Lovastatin
 | n* | Dose | Lp(a) | n* | Dose | Lp(a) | n* | Dose | Lp(a)
 |  | (mg/mg) |  |  | (mg) |  |  | (mg)
Baseline | 57 | – | 34 mg/dL | 61 | – | 41 mg/dL | 60 | – | 42 mg/dL
12 | 47 | 1000/20 | -9% | 46 | 1000 | -8% | 55 | 20 | +8%
16 | 45 | 1000/40 | -9% | 44 | 1000 | -12% | 55 | 40 | +8%
20 | 42 | 1500/40 | -17% | 43 | 1500 | -22% | 53 | 40 | +6%
28 | 42 | 2000/40 | -22% | 41 | 2000 | -32% | 52 | 40 | 0%
* n = number of patients remaining in trial at each time point

14.4 NIASPAN and Simvastatin Clinical Studies

In a double-blind, randomized, multicenter, multi-national, active-controlled, 24-week study, the lipid effects of a combination tablet of NIASPAN and simvastatin were compared to simvastatin 20 mg and 80 mg in 641 patients with type II hyperlipidemia or mixed dyslipidemia. Following a lipid qualification phase, patients were eligible to enter one of two treatment groups. In Group A, patients on simvastatin 20 mg monotherapy, with elevated non-HDL levels and LDL-C levels at goal per the NCEP guidelines, were randomized to one of three treatment arms: combination tablet of NIASPAN and simvastatin 1000/20 mg, combination tablet of NIASPAN and simvastatin 2000/20 mg, or simvastatin 20 mg. In Group B, patients on simvastatin 40 mg monotherapy, with elevated non-HDL levels per the NCEP guidelines regardless of attainment of LDL-C goals, were randomized to one of three treatment arms: combination tablet of NIASPAN and simvastatin 1000/40 mg, combination tablet of NIASPAN and simvastatin 2000/40 mg, or simvastatin 80 mg. Therapy was initiated at the 500 mg dose of combination tablet of NIASPAN and simvastatin and increased by 500 mg every four weeks. Thus patients were titrated to the 1000 mg dose of combination tablet of NIASPAN and simvastatin after four weeks and to the 2000 mg dose of combination tablet of NIASPAN and simvastatin after 12 weeks. All patients randomized to simvastatin monotherapy received 50 mg immediate-release niacin daily in an attempt to keep the study from becoming unblinded due to flushing in the combination tablet of NIASPAN and simvastatin groups. Patients were instructed to take one 325 mg aspirin or 200 mg ibuprofen 30 minutes prior to taking the double-blind medication to help minimize flushing effects.

In Group A, the primary efficacy analysis was a comparison of the mean percent change in non-HDL levels between the combination tablet of NIASPAN and simvastatin 2000/20 mg and simvastatin 20 mg groups, and if statistically significant, then a comparison was conducted between the combination tablet of NIASPAN and simvastatin 1000/20 mg and simvastatin 20 mg groups. In Group B, the primary efficacy analysis was a determination of whether the mean percent change in non-HDL in the combination tablet of NIASPAN and simvastatin 2000/40 mg group was non-inferior to the mean percent change in the simvastatin 80 mg group, and if so, whether the mean percent change in non-HDL in the combination tablet of NIASPAN and simvastatin 1000/40 mg group was non-inferior to the mean percent change in the simvastatin 80 mg group.

In Group A, the non-HDL-C lowering with combination tablet of NIASPAN and simvastatin 2000/20 and combination tablet of NIASPAN and simvastatin 1000/20 was statistically significantly greater than that achieved with simvastatin 20 mg after 24 weeks (<0.05;). The completion rate after 24 weeks was 72% for the combination tablet of NIASPAN and simvastatin arms and 88% for the simvastatin 20 mg arm. In Group B, the non-HDL-C lowering with combination tablet of NIASPAN and simvastatin 2000/40 and combination tablet of NIASPAN and simvastatin 1000/40 was non-inferior to that achieved with simvastatin 80 mg after 24 weeks (). The completion rate after 24 weeks was 78% for the combination tablet of NIASPAN and simvastatin arms and 80% for the simvastatin 80 mg arm. p Table 12 Table 13

The combination tablet of NIASPAN and simvastatin was not superior to simvastatin in lowering LDL-C in either Group A or Group B. However, the combination tablet of NIASPAN and simvastatin was superior to simvastatin in both groups in lowering TG and raising HDL (Tables and). 1415

Table 12. Non-HDL Treatment Response Following 24-Week Treatment Mean Percent Change from Simvastatin 20-mg Treated Baseline
Group A
 | Combination Tablet of NIASPAN and Simvastatin 2000/20 |  |  | Combination Tablet of NIASPAN and Simvastatin 1000/20 |  |  | Simvastatin 20
Week | na | Dose (mg/mg) | Non-HDLb | na | Dose (mg/mg) | Non-HDLb | na | Dose (mg/mg) | Non-HDLb
Baseline | 56 | – | 163.1 mg/dL | 108 | – | 164.8 mg/dL | 102 | – | 163.7 mg/dL
4 | 52 | 500/20 | -12.9% | 86 | 500/20 | -12.8% | 91 | 20 | -8.3%
8 | 46 | 1000/20 | -17.5% | 91 | 1000/20 | -15.5% | 95 | 20 | -8.3%
12 | 46 | 1500/20 | -18.9% | 90 | 1000/20 | -14.8% | 96 | 20 | -6.4%
24 | 40 | 2000/20 | -19.5%† | 78 | 1000/20 | -13.6%† | 90 | 20 | -5.0%
Dropouts by week 24: | 28.6% |  |  | 27.8% |  |  | 11.8%
n=number of subjects with values in the analysis window at each timepoint The percent change from baseline is the model-based mean from a repeated measures mixed model with no imputation for missing data from study dropouts. significant vs. simvastatin 20 mg at the primary endpoint (Week 24), <0.05a
b
† p

Table 13. Non-HDL Treatment Response Following 24-Week Treatment Mean Percent Change from Simvastatin 40-mg Treated Baseline
Group B
 | Combination Tablet of NIASPAN and Simvastatin 2000/40 |  |  | Combination Tablet of NIASPAN and Simvastatin 1000/40 |  |  | Simvastatin 80
Week | na | Dose (mg/mg) | Non-HDLb | na | Dose (mg/mg) | Non-HDLb | na | Dose (mg/mg) | Non-HDLb
Baseline | 98 | – | 144.4 mg/dL | 111 | – | 141.2 mg/dL | 113 | – | 134.5 mg/dL
4 | 96 | 500/40 | -6.0% | 108 | 500/40 | -5.9% | 110 | 80 | -11.3%
8 | 93 | 1000/40 | -15.5% | 100 | 1000/40 | -16.2% | 104 | 80 | -13.7%
12 | 90 | 1500/40 | -18.4% | 97 | 1000/40 | -12.6% | 100 | 80 | -9.5%
24 | 80 | 2000/40 | -7.6%c | 82 | 1000/40 | -6.7%d | 90 | 80 | -6.0%
Dropouts by week 24: | 18.4% |  |  | 26.1% |  |  | 20.4%
n=number of subjects with values in the analysis window at each timepoint The percent change from baseline is the model-based mean from a repeated measures mixed model with no imputation for missing data from study dropouts. non-inferior to simvastatin 80 arm; 95% confidence interval of mean difference in non-HDL for the combination tablet of NIASPAN and simvastatin 2000/40 vs. simvastatin 80 is (-7.7%, 4.5%) non-inferior to simvastatin 80 arm; 95% confidence interval of mean difference in non-HDL for combination tablet of NIASPAN and simvastatin 1000/40 vs. combination tablet of NIASPAN and simvastatin 80 is (-6.6%, 5.3%)a
b
c
d

Table 14. Mean Percent Change from Baseline to Week 24 in Lipoprotein Lipid Levels
Treatment Group A
TREATMENT | N | LDL-C | Total-C | HDL-C | TGa | Apo B
Baseline (mg/dL)* | 266 | 120 | 207 | 43 | 209 | 102
Simvastatin 20 mg | 102 | -6.7% | -4.5% | 7.8% | -15.3% | -5.6%
Combination Tablet of NIASPAN and Simvastatin 1000/20 | 108 | -11.9% | -8.8% | 20.7% | -26.5% | -13.2%
Combination Tablet of NIASPAN and Simvastatin 2000/20 | 56 | -14.3% | -11.1% | 29.0% | -38.0% | -18.5%
either treatment naïve or after receiving simvastatin 20 mg medians are reported for TG*
a

Table 15. Mean Percent Change from Baseline to Week 24 in Lipoprotein Lipid Levels
Treatment Group B
TREATMENT | N | LDL-C | Total-C | HDL-C | TGa | Apo B
Baseline (mg/dL)* | 322 | 108 | 187 | 47 | 145 | 93
Simvastatin 80 mg | 113 | -11.4% | -6.2% | 0.1% | 0.3% | -7.5%
Combination Tablet of NIASPAN and Simvastatin 1000/40 | 111 | -7.1% | -3.1% | 15.4% | -22.8% | -7.7%
Combination Tablet of NIASPAN and Simvastatin 2000/40 | 98 | -5.1 | -1.6% | 24.4% | -31.8% | -10.5%
after receiving simvastatin 40 mg medians are reported for TG*
a

16 HOW SUPPLIED/STORAGE AND HANDLING

NDC:68151-4069-9 in a PACKAGE of 1 TABLET, FILM COATED, EXTENDED RELEASES

17 PATIENT COUNSELING INFORMATION

17.1 Patient Counseling

Patients should be advised to adhere to their National Cholesterol Education Program (NCEP) recommended diet, a regular exercise program, and periodic testing of a fasting lipid panel.

Patients should be advised to inform other healthcare professionals prescribing a new medication that they are taking NIASPAN.

The patient should be informed of the following:

Dosing Time

NIASPAN tablets should be taken at bedtime, after a low-fat snack. Administration on an empty stomach is not recommended.

Tablet Integrity

NIASPAN tablets should not be broken, crushed or chewed, but should be swallowed whole.

Dosing Interruption

If dosing is interrupted for any length of time, their physician should be contacted prior to restarting therapy; re-titration is recommended.

Muscle Pain

Notify their physician of any unexplained muscle pain, tenderness, or weakness promptly. They should discuss all medication, both prescription and over the counter, with their physician.

Flushing

Flushing (warmth, redness, itching and/or tingling of the skin) is a common side effect of niacin therapy that may subside after several weeks of consistent NIASPAN use. Flushing may vary in severity and is more likely to occur with initiation of therapy, or during dose increases. By dosing at bedtime, flushing will most likely occur during sleep. However, if awakened by flushing at night, the patient should get up slowly, especially if feeling dizzy, feeling faint, or taking blood pressure medications. Advise patients of the symptoms of flushing and how they differ from the symptoms of a myocardial infarction.

Use of Aspirin Medication

Taking aspirin (up to the recommended dose of 325 mg) approximately 30 minutes before dosing can minimize flushing.

Diet

Avoid ingestion of alcohol, hot beverages and spicy foods around the time of taking NIASPAN to minimize flushing.

Supplements

Notify their physician if they are taking vitamins or other nutritional supplements containing niacin or nicotinamide.

Dizziness

Notify their physician if symptoms of dizziness occur.

Diabetics

If diabetic, to notify their physician of changes in blood glucose.

Pregnancy

Discuss future pregnancy plans with your patients, and discuss when to stop NIASPAN if they are trying to conceive. Patients should be advised that if they become pregnant, they should stop taking NIASPAN and call their healthcare professional.

Breastfeeding

Women who are breastfeeding should be advised to not use NIASPAN. Patients, who have a lipid disorder and are breastfeeding, should be advised to discuss the options with their healthcare professional.

© AbbVie Inc. 2013

Manufactured for AbbVie Inc., North Chicago, IL 60064, U.S.A.

500 mg tablets

by Norwich Pharmaceuticals, Inc., Norwich, NY 13815

or

500 mg, 750 mg and 1000 mg tablets

by AbbVie LTD, Barceloneta, PR 00617

03-A751 March, 2013

PATIENT INFORMATION

NIASPAN® (ny-a-span)

(niacin extended-release) tablets

Read this information carefully before you start taking NIASPAN and each time you get a refill. There may be new information. This information does not take the place of talking with your doctor about your medical condition or your treatment.

What is NIASPAN?

NIASPAN is a prescription medicine used with diet and exercise to increase the good cholesterol (HDL) and lower the bad cholesterol (LDL) and fats (triglycerides) in your blood.

- NIASPAN can be used by itself or with other cholesterol-lowering medicines.
- NIASPAN is also used to lower the risk of heart attack in people who have had a heart attack and have high cholesterol.
- In people with coronary artery disease and high cholesterol, NIASPAN, when used with a bile acid-binding resin (another cholesterol medicine) can slow down or lessen the build-up of plaque (fatty deposits) in your arteries.
- In people with heart problems and well-controlled cholesterol, taking NIASPAN with another cholesterol-lowering medicine (simvastatin) has not been shown to reduce heart attacks or strokes more than taking simvastatin alone.

It is not known if NIASPAN is safe and effective in children 16 years of age and under.

Who should not take NIASPAN?

Do not take NIASPAN if you have:

- liver problems
- a stomach ulcer
- bleeding problems
- an allergy to niacin or any of the ingredients in NIASPAN. See the end of this leaflet for a complete list of ingredients in NIASPAN.

What should I tell my doctor before taking NIASPAN?

Before you take NIASPAN, tell your doctor, if you:

- have diabetes. Tell your doctor if your blood sugar levels change after you take NIASPAN.
- have gout
- have kidney problems
- are pregnant or plan to become pregnant. It is not known if NIASPAN will harm your unborn baby. Talk to your doctor if you are pregnant or plan to become pregnant while taking NIASPAN.
- are breastfeeding or plan to breastfeed. NIASPAN can pass into your breast milk. You and your doctor should decide if you will take NIASPAN or breastfeed. You should not do both. Talk to your doctor about the best way to feed your baby if you take NIASPAN.

including prescription and non-prescription medicines, vitamins, herbal supplements or other nutritional supplements containing niacin or nicotinamide. NIASPAN and other medicines may affect each other causing side effects. NIASPAN may affect the way other medicines work, and other medicines may affect how NIASPAN works. Tell your doctor about all the medicines you take,

Especially tell your doctor if you take:

- other medicines to lower cholesterol or triglycerides
- aspirin
- blood pressure medicines
- blood thinner medicines
- large amounts of alcohol

Know the medicines you take. Keep a list of them to show your doctor and pharmacist when you get a new medicine.

How should I take NIASPAN?

- Take NIASPAN exactly as your doctor tells you to take it.
- Take NIASPAN tablets whole. Do not break, crush or chew NIASPAN tablets before swallowing.
- Take NIASPAN 1 time a day at bedtime after a low-fat snack. NIASPAN should not be taken on an empty stomach.
- All forms of niacin are not the same as NIASPAN. Do not switch between forms of niacin without first talking to your doctor as severe liver damage can occur.
- Do not change your dose or stop taking NIASPAN unless your doctor tells you to.
- If you need to stop taking NIASPAN, call your doctor before you start taking NIASPAN again. Your doctor may need to lower your dose of NIASPAN.
- If you forget to take a dose of NIASPAN, take it as soon as you remember.
- If you take too much NIASPAN, call your doctor right away.
- Medicines used to lower your cholesterol called bile acid resins, such as colestipol and cholestyramine, should not be taken at the same time of day as NIASPAN. You should take NIASPAN and the bile acid resin medicine at least 4 to 6 hours apart.
- Your doctor may do blood tests before you start taking NIASPAN and during your treatment. You should see your doctor regularly to check your cholesterol and triglyceride levels and to check for side effects.

What are the possible side effects of NIASPAN?

NIASPAN may cause serious side effects, including:

- severe liver problems. Signs of liver problems include:
  - increased tiredness
  - dark colored urine (tea-colored)
  - loss of appetite
  - light colored stools
  - nausea
  - right upper stomach (abdomen) pain
  - yellowing of your skin or whites of your eye
  - itchy skin

- unexplained muscle pain, tenderness or weakness
- high blood sugar level (glucose)

Call your doctor right away if you have any of the side effects listed above.

The most common side effects of NIASPAN include:

- flushing
- diarrhea
- nausea
- vomiting
- increased cough
- rash

Flushing happens when tiny blood vessels near the surface of the skin (especially on the face, neck, chest and/or back) open wider. Symptoms of flushing may include any or all of the following: Flushing is the most common side effect of NIASPAN.

- warmth
- redness
- itching
- tingling of the skin

Flushing does not always happen. If it does, it is usually within 2 to 4 hours after taking a dose of NIASPAN. Flushing may last for a few hours. Flushing is more likely to happen when you first start taking NIASPAN or when your dose of NIASPAN is increased. Flushing may get better after several weeks.

If you wake up at night because of flushing, get up slowly, especially if you:

- feel dizzy or faint
- take blood pressure medicines

To lower your chance of flushing:

- Ask your doctor if you can take aspirin to help lower the flushing side effect from NIASPAN. You can take aspirin (up to the recommended dose of 325 mg) about 30 minutes before you take NIASPAN to help lower the flushing side effect.
- Do not drink hot beverages (including coffee), alcohol, or eat spicy foods around the time you take NIASPAN.
- Take NIASPAN with a low-fat snack to lessen upset stomach.

People with high cholesterol and heart disease are at risk for a heart attack. Symptoms of a heart attack may be different from a flushing reaction from NIASPAN. The following may be symptoms of a heart attack due to heart disease and not a flushing reaction:

- chest pain
- pain in other areas of your upper body such as one or both arms, back, neck, jaw or stomach
- shortness of breath
- sweating
- nausea
- lightheadedness

The chest pain you have with a heart attack may feel like uncomfortable pressure, squeezing, fullness or pain that lasts more than a few minutes, or that goes away and comes back. Heart attacks may be sudden and intense, but often start slowly, with mild pain or discomfort.

Call your doctor right away if you have any symptoms of a heart attack.

Tell your doctor if you have any side effect that bothers you or does not go away.

These are not all the possible side effects of NIASPAN. For more information, ask your doctor or pharmacist.

Call your doctor for medical advice about side effects. You may report side effects to FDA at 1-800-FDA-1088.

How should I store NIASPAN?

- Store NIASPAN at 68ºF to 77ºF (20ºC to 25ºC).

Keep NIASPAN and all medicines out of the reach of children.

General information about the safe and effective use of NIASPAN.

Medicines are sometimes prescribed for purposes other than those listed in a Patient Information leaflet. Do not use NIASPAN for a condition for which it was not prescribed. Do not give NIASPAN to other people, even if they have the same symptoms that you have. It may harm them.

This leaflet summarizes the most important information about NIASPAN. If you would like more information, talk with your doctor. You can ask your pharmacist or doctor for information about NIASPAN that is written for health professionals.

For more information, go to www.NIASPAN.com or call AbbVie Inc. Medical Information at 1-800-633-9110.

What are the ingredients in NIASPAN?

niacin Active ingredient:

hypromellose, povidone, stearic acid, and polyethylene glycol, and the following coloring agents: FD&C yellow #6/sunset yellow FCF Aluminum Lake, synthetic red and yellow iron oxides, and titanium dioxide Inactive Ingredients:

This Patient Information has been approved by the U.S. Food and Drug Administration.

Manufactured for AbbVie Inc., North Chicago, IL 60064, U.S.A.

500 mg tablets by Norwich Pharmaceuticals, Inc., Norwich, NY 13815

or 500 mg, 750 mg and 1000 mg tablets

by AbbVie LTD, Barceloneta, PR 00617

Revised: 03/2013 AbbVie Inc.